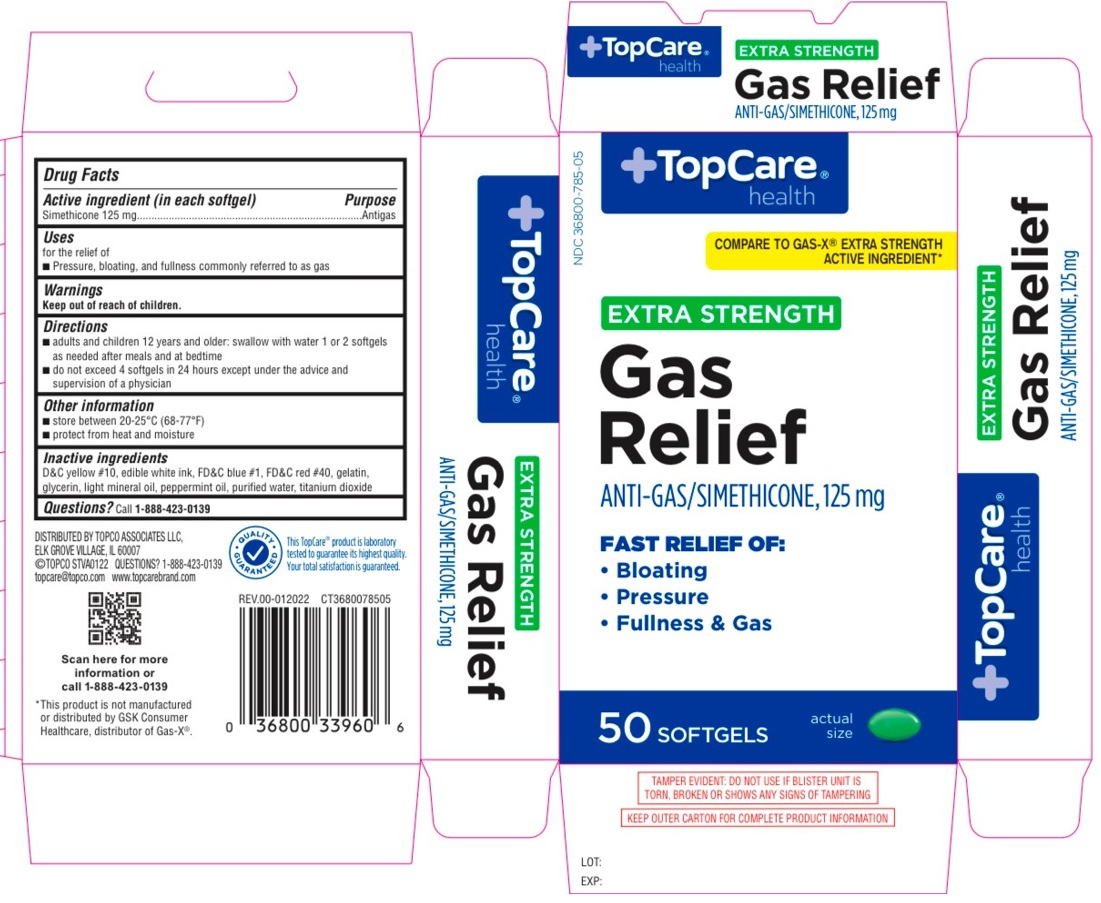 DRUG LABEL: Gas Relief Extra Strength
NDC: 36800-785 | Form: CAPSULE, LIQUID FILLED
Manufacturer: TOPCO ASSOCIATES LLC
Category: otc | Type: HUMAN OTC DRUG LABEL
Date: 20241214

ACTIVE INGREDIENTS: DIMETHICONE, UNSPECIFIED 125 mg/1 1
INACTIVE INGREDIENTS: D&C YELLOW NO. 10; FD&C BLUE NO. 1; FD&C RED NO. 40; GELATIN, UNSPECIFIED; GLYCERIN; LIGHT MINERAL OIL; PEPPERMINT OIL; WATER; TITANIUM DIOXIDE

Gas Relief Extra Strength

Drug Facts

Active ingredient (in each softgel)

Simethicone 125 mg

Purpose

Antigas

Uses

for the relief of
• Pressure, bloating, and fullness commonly referred to as gas

Warnings

Keep out of reach of children.

Directions

- adults and children 12 years and older: swallow with water 1 or 2 softgels as needed after meals and at bedtime
- do not exceed 4 softgels in 24 hours except under the advice and supervision of a physician

Other information

- store between 20-25°C (68-77°F)
- protect from heat and moisture

Inactive ingredients

D&C yellow #10, edible white ink, FD&C blue #1, FD&C red #40, gelatin. glycerin, light mineral oil, peppermint oil, purified water, titanium dioxide

Questions?

Call 1-888-423-0139

TopCare® health

COMPARE TO GAS-X® EXTRA STRENGTH ACTIVE INGREDIENT*

FAST RELIEF OF:

- Bloating
- Pressure
- Fullness & Gas

DISTRIBUTED BY TOPCO ASSOCIATES LLC,
ELK GROVE VILLAGE, IL 60007
©TOPCO STVA0122
topcare@topco.com www.topcarebrand.com

This TopCare® product is laboratory tested to guarantee its highest quality. Your total satisfaction is guaranteed.

*This product is not manufactured or distributed by GSK Consumer Healthcare, distributor of Gas-X®.

TAMPER EVIDENT: DO NOT USE IF BLISTER UNIT IS TORN, BROKEN OR SHOWS ANY SIGNS OF TAMPERING

KEEP OUTER CARTON FOR COMPLETE PRODUCT INFORMATION